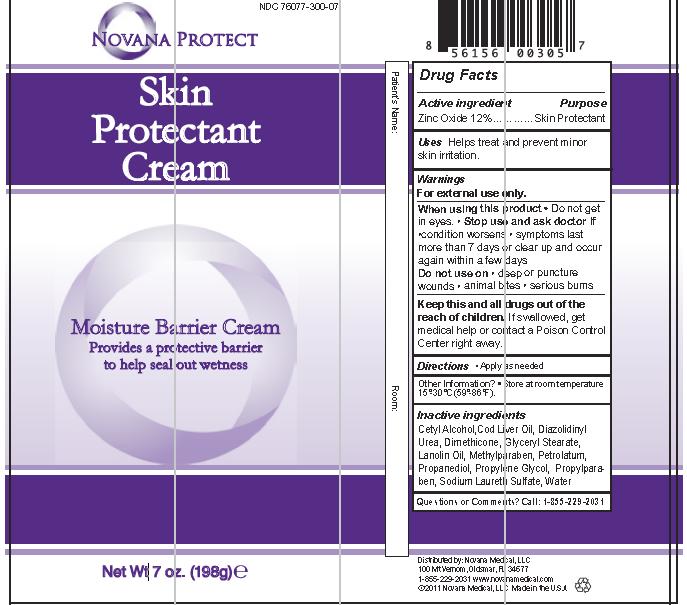 DRUG LABEL: Novana Protect Barrier
NDC: 76077-300 | Form: CREAM
Manufacturer: NOVANA MEDICAL LLC
Category: otc | Type: HUMAN OTC DRUG LABEL
Date: 20120404

ACTIVE INGREDIENTS: Zinc Oxide .12 mL/1 mL
INACTIVE INGREDIENTS: Water; Lanolin; Cetyl Alcohol; Glyceryl Monostearate; Cod Liver Oil; Petrolatum; Propanediol; Sodium Laureth Sulfate; Propylene Glycol; Diazolidinyl Urea; Methylparaben; Propylparaben; Dimethicone

Drug Facts

Active ingredient Purpose
Zinc Oxide 12%...............................Skin Protectant

Warnings

For external use only.

When using this product • Do not get in eyes. Stop use and ask doctor if •condition worsens • symptoms last more than 7 days or clear up and occur again within a few days. Do not use on • deep or puncture wounds • animal bites • serious burns

KEEP OUT OF REACH OF CHILDREN

Keep this and all drugs out of the reach of children. If swallowed, get medical help or contact a Poison Control Center right away.

INSTRUCTIONS FOR USE

Directions • Apply as needed

Inactive ingredients
Cetyl Alcohol,Cod Liver Oil, Diazolidinyl Urea, Dimethicone, Glyceryl Stearate, Lanolin Oil, Methylparaben, Petrolatum, Propanediol, Propylene Glycol, Propylparaben, Sodium Laureth Sulfate, Water